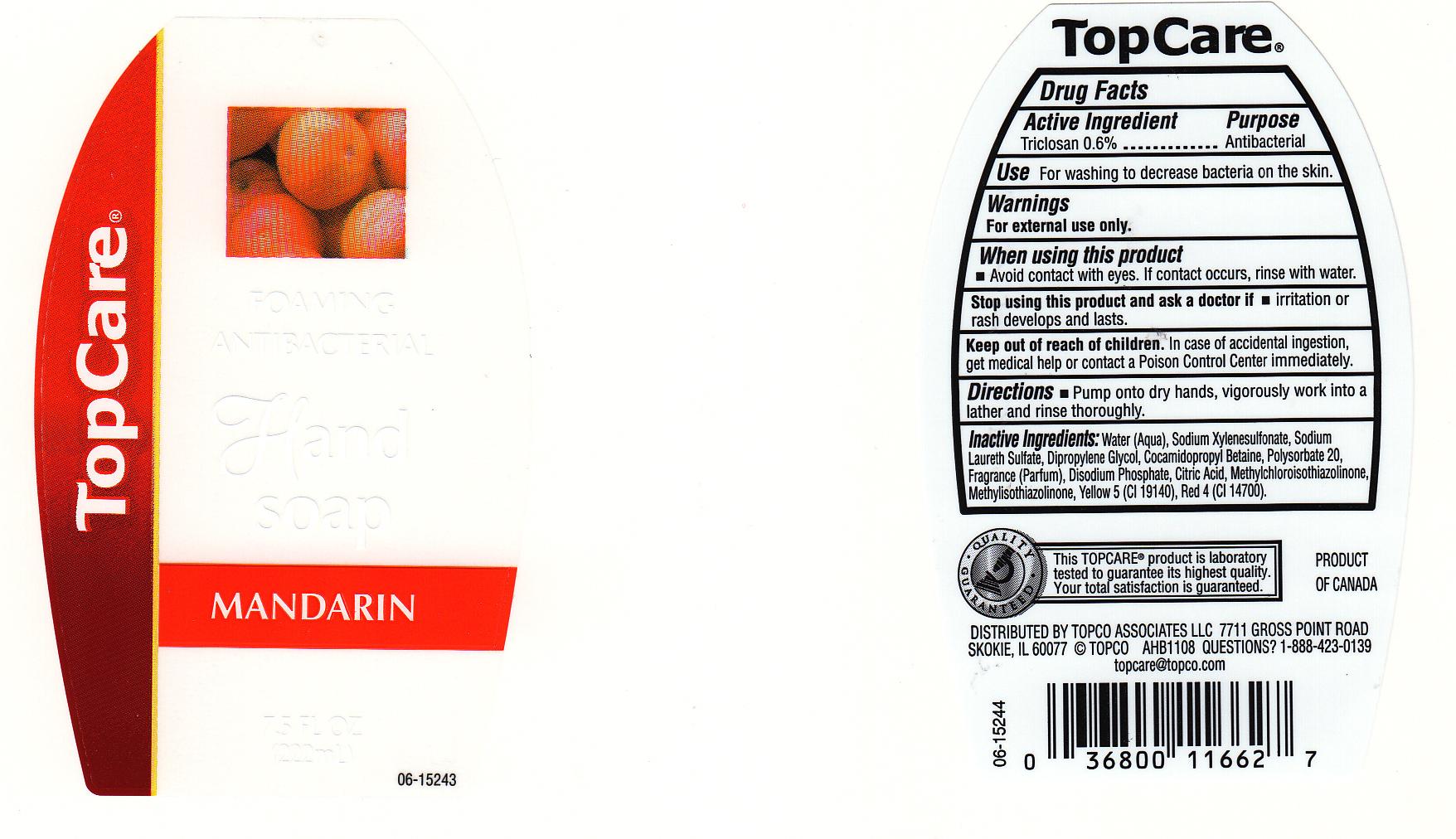 DRUG LABEL: ANTIBACTERIAL
NDC: 36800-066 | Form: SOLUTION
Manufacturer: TOPCO ASSOCIATES L LLC
Category: otc | Type: HUMAN OTC DRUG LABEL
Date: 20110823

ACTIVE INGREDIENTS: TRICLOSAN 0.6 mL/100 mL
INACTIVE INGREDIENTS: WATER; SODIUM XYLENESULFONATE; DIPROPYLENE GLYCOL; SODIUM LAURETH SULFATE; COCAMIDOPROPYL BETAINE; SODIUM PHOSPHATE, DIBASIC; ANHYDROUS CITRIC ACID; FD&C RED NO. 4; FD&C YELLOW NO. 5; POLYSORBATE 20; METHYLCHLOROISOTHIAZOLINONE; METHYLISOTHIAZOLINONE

DRUG FACTS BOX

ACTIVE INGREDIENT

TRICLOSAN 0.6%

PURPOSE

ANTIBACTERIAL

USES

FOR WASHING TO HELP DECREASE BACTERIA ON THE SKIN.

WARNINGS

FOR EXTERNAL USE ONLY

WHEN USING THIS PRODUCT

AVOID CONTACT WITH EYES. IF CONTACT OCCURS, RINSE THOROUGHLY WITH WATER.

STOP USING THIS PRODUCT AND ASK A DOCTOR IF

IRRITATION OR RASH DEVELOPS AND LASTS.

KEEP OUT OF REACH OF CHILDREN

IN CASE OF ACCIDENTAL INGESTION, GET MEDICAL HELP OR CONTACT POISON CONTROL CENTER IMMEDIATELY

DIRECTIONS

PUMP ONTO DRY HANDS, VIGOROUSLY WORK INTO A LATHER AND RINSE THOROUGHLY.

INACTIVE INGREDIENTS

WATER, SODIUM XYLENESULFONATE, SODIUM LAURETH SULFATE, DIPROPYLENE GLYCOL, COCAMIDOPROPYL BETAINE, POLYSORBATE 20, FRAGRANCE, DISODIUM PHOSPHATE, CITRIC ACID, METHYLCHLOROISOTHIAZOLINONE, METHYLISOTHIAZOLINONE, YELLOW 5 (CI 19140), RED (CI 14700).